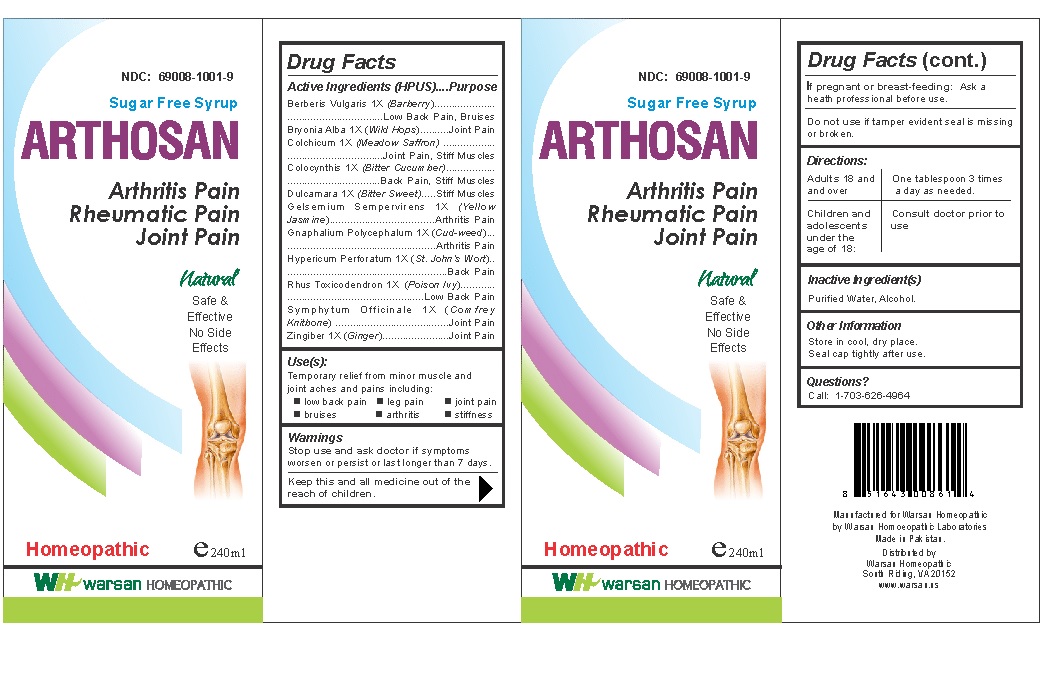 DRUG LABEL: Arthosan
NDC: 69008-1001 | Form: SOLUTION/ DROPS
Manufacturer: Warsan Homoeopathic
Category: homeopathic | Type: HUMAN OTC DRUG LABEL
Date: 20180219

ACTIVE INGREDIENTS: HYPERICUM PERFORATUM 1 [hp_X]/1 mL; PSEUDOGNAPHALIUM OBTUSIFOLIUM 1 [hp_X]/1 mL; TOXICODENDRON PUBESCENS LEAF 1 [hp_X]/1 mL; COMFREY ROOT 1 [hp_X]/1 mL; COLCHICUM AUTUMNALE BULB 1 [hp_X]/1 mL; BERBERIS VULGARIS ROOT BARK 1 [hp_X]/1 mL; SOLANUM DULCAMARA TOP 1 [hp_X]/1 mL; GELSEMIUM SEMPERVIRENS ROOT 1 [hp_X]/1 mL; BRYONIA ALBA ROOT 1 [hp_X]/1 mL; CITRULLUS COLOCYNTHIS FRUIT PULP 1 [hp_X]/1 mL; GINGER 1 [hp_X]/1 mL
INACTIVE INGREDIENTS: WATER; ALCOHOL

Keep out of reach of children.

Stop use and ask doctor if symptoms worsen or persist longer than 7 days.

If pregnant or breast-feeding, ask health professional before use.

Do not use if tamper evident seal is missing or broken.

ACTIVE INGREDIENT

Berberis Vulgaris 1X
Bryonia Alba 1X
Colchicum 1X
Colocynthis 1X
Dulcamara 1X
Gelsemium Sempervirens 1X
Gnaphalium Polycephalum 1X
Hypericum Perforatum 1X
Rhus Toxicodendron 1X
Symphytum Officinale 1X
Zingiber 1X

PURPOSE

Temporary relief from minor muscle and joint aches and pains including: low back pain, leg pain, joint pain, bruises, arthritis, stiffness.

INACTIVE INGREDIENT

Purified Water

Alcohol

DOSAGE AND ADMINISTRATION

Adults and children 18 years and older: One tablespoon three times daily.

Children and adolescents under the age of 18: Consult doctor prior to use.

INDICATIONS AND USAGE

Temporary relief from minor muscle and joint aches and pains including: low back pain, leg pain, joint pain, bruises, arthritis, stiffness.